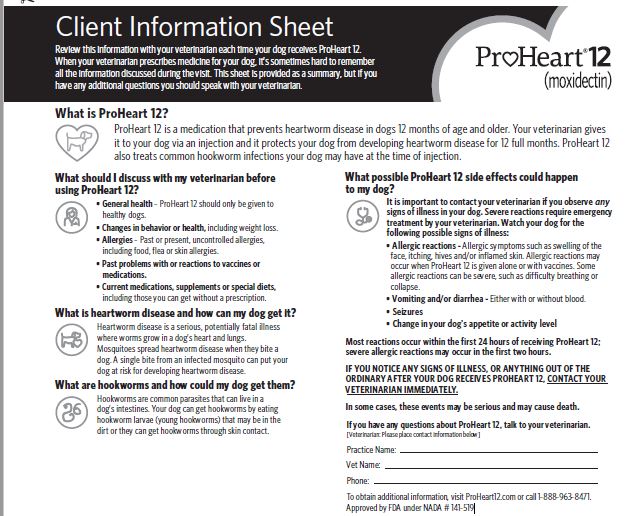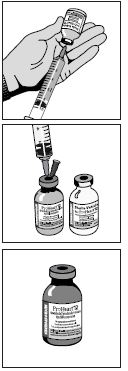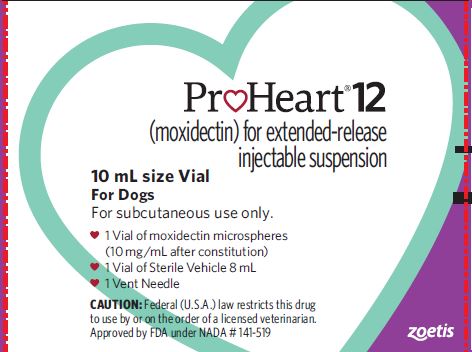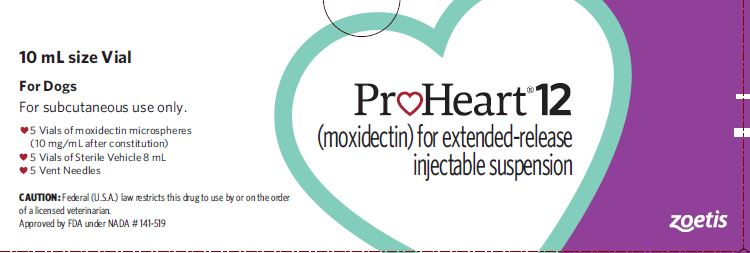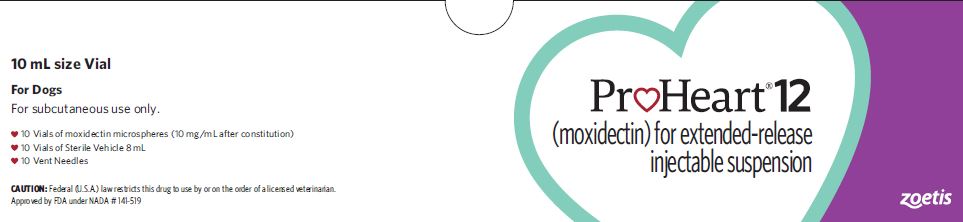 DRUG LABEL: ProHeart 12
NDC: 54771-0256 | Form: KIT | Route: SUBCUTANEOUS
Manufacturer: Zoetis Inc.
Category: animal | Type: PRESCRIPTION ANIMAL DRUG LABEL
Date: 20220323

ACTIVE INGREDIENTS: MOXIDECTIN 10 mg/1 mL
INACTIVE INGREDIENTS: TRISTEARIN; BUTYLATED HYDROXYTOLUENE

ProHeart® 12 (moxidectin)
For Extended-Release Injectable Suspension for Dogs

CAUTION

Federal (U.S.A.) law restricts this drug to use by or on the order of a licensed veterinarian.

DESCRIPTION

ProHeart 12 (moxidectin) for extended-release injectable suspension consists of two separate vials: one vial contains 10% moxidectin sterile microspheres; and the second vial contains a specifically formulated sterile vehicle for constitution with the microspheres. A clear or translucent appearance of the vehicle is normal. Each mL of constituted drug product contains 10 mg moxidectin, 9% glyceryl tristearate, 2.25% hydroxypropyl methylcellulose, 0.81% sodium chloride, 0.16% methylparaben, 0.02% propylparaben and 0.004% butylated hydroxytoluene. Hydrochloric acid is used to adjust pH. The constituted product may appear as a hazy to milky suspension.

INDICATIONS

ProHeart 12 is indicated for use in dogs 12 months of age and older for the prevention of heartworm disease caused by Dirofilaria immitis for 12 months.
ProHeart 12 is indicated for the treatment of existing larval and adult hookworm (Ancylostoma caninum and Uncinaria stenocephala) infections.

DOSAGE AND ADMINISTRATION

Always provide Client Information Sheet and review with owners before administering ProHeart 12. The owner should be advised to observe their dog for adverse drug events including those described on the sheet. The Client Information Sheet is attached to this package insert and available online at http://www.proheart12.com for reprinting to provide to the owner.

Frequency of Treatment:

ProHeart 12 prevents the development of heartworm disease caused by D. immitis for 12 months. For dogs not previously on heartworm preventive or having lapsed beyond 12 months of a prior ProHeart 12 dose, the product should be given within 1 month of exposure to mosquitoes. Follow-up treatments may be given every 12 months, if the dog continues to be healthy and without weight loss, to provide continuous year-round protection. When replacing a monthly heartworm preventive product, ProHeart 12 should be given within one month of the last dose of the former medication to avoid a gap in protection.

ProHeart 12 eliminates the larval and adult stages of A. caninum and U. stenocephala present at the time of treatment. Re-infection with A. caninum and U. stenocephala may occur sooner than 12 months.

Dose:

The recommended subcutaneous dose is 0.05 mL of the constituted suspension/kg body weight (0.023 mL/lb). This amount of suspension will provide 0.5 mg moxidectin/kg body weight (0.23 mg/lb). To ensure accurate dosing, calculate each dose based on the dog’s weight at the time of treatment. The following table provides a guide for weight specific dose volumes.

Table 1: Dosage Guide

Dog Weight |  | Dose Volume*; mL/Dog
Pounds (lb) | Kilograms (kg)
11 lb | 5 kg | 0.25
22 lb | 10 kg | 0.50
33 lb | 15 kg | 0.75
44 lb | 20 kg | 1.00
55 lb | 25 kg | 1.25
66 lb | 30 kg | 1.50
77 lb | 35 kg | 1.75
88 lb | 40 kg | 2.00
99 lb | 45 kg | 2.25
110 lb | 50 kg | 2.50
121 lb | 55 kg | 2.75
132 lb | 60 kg | 3.00

*All dogs should be dosed at 0.05 mL suspension/kg body weight (0.023 mL /lb).

Injection Technique:

ProHeart 12 must be prepared at least 30 minutes prior to the first use by adding the sterile vehicle to the microspheres. (See CONSTITUTION PROCEDURES for initial mixing instructions.)

Swirl the constituted product vial gently before every use to uniformly re-suspend the microspheres.
Withdraw 0.05 mL of suspension/kg body weight (0.023 mL/lb) into an appropriately sized syringe fitted with an 18G or 20G hypodermic needle. Dose promptly after drawing into dosing syringe. If administration is delayed, gently roll the dosing syringe prior to injection to maintain a uniform suspension and accurate dosing.

Using aseptic technique, inject the product subcutaneously in the left or right side of the dorsum of the neck cranial to the scapula. No more than 3 mL should be administered in a single site. The location(s) of each injection (left or right side) should be noted so that prior injection sites can be identified and the next injection can be administered on the opposite side.

RISK MINIMIZATION ACTION PLAN

The ProHeart 12 and ProHeart 6 Risk Minimization Action Plan (RiskMAP) provides educational materials to the veterinarian, veterinary staff, and the dog owner explaining the risks and proper use of ProHeart 12 and ProHeart 6. ProHeart 12 and ProHeart 6 are the same formulation, but ProHeart 12 is three times the concentration of ProHeart 6. ProHeart 12 and ProHeart 6 are for use in dogs only and are available through a restricted distribution program to veterinarians that have completed the RiskMAP training and certification module.

The ProHeart 12 and ProHeart 6 web-based training and certification module is available at http://www.proheart12.com. This website has important information on the safe and effective use of ProHeart 12 and ProHeart 6 for veterinarians.

Only veterinarians and veterinary technicians/assistants that have completed the training and are certified can administer ProHeart 12 and ProHeart 6.

Veterinarians are expected to report all adverse events that occur in animals or humans to the manufacturer. Important safety information is included below:

CONTRAINDICATIONS

ProHeart 12 is contraindicated in animals previously found to be hypersensitive to this drug or ProHeart 6.

HUMAN WARNINGS

Not for human use. Keep this and all drugs out of the reach of children.
If contact with your skin occurs, wash thoroughly with water. May be irritating to the eyes. If product accidentally gets into your eyes, flush eyes thoroughly with water. In case of accidental ingestion, or if skin or eye irritation occurs, contact a Poison Control Center or physician for treatment advice and show the package insert to the physician.
Take care to avoid accidental self-injection. In case of accidental self-injection, seek medical advice and show the package insert or the label to the physician. The Safety Data Sheet (SDS) contains more detailed occupational safety information.

WARNINGS

Anaphylactic and anaphylactoid reactions may occur in some dogs following administration of ProHeart 12 alone or with vaccines. In some cases, these reactions have resulted in death following administration of moxidectin microspheres (see POST-APPROVAL EXPERIENCE). Anaphylactic and anaphylactoid reactions should be treated immediately with the same measures used to treat hypersensitivity reactions to vaccines and other injectable products.

Always provide Client Information Sheet and review with owners before administering ProHeart 12. The owner should be advised to observe their dog for adverse drug events including those described on the sheet.

Do not administer ProHeart 12 to dogs who are sick, debilitated, underweight or who have a history of weight loss.

PRECAUTIONS

Prior to administration of ProHeart 12, the health of the patient should be assessed by a thorough medical history, physical examination and diagnostic testing as indicated (see WARNINGS).

Caution should be used when administering ProHeart 12 in dogs with pre-existing allergic disease, including food allergy, atopy, and flea allergy dermatitis. (see WARNINGS).

Caution should be used when administering ProHeart 12 concurrently with vaccinations. Adverse reactions, including anaphylaxis, have been reported following the concomitant use of moxidectin microspheres and vaccinations (see WARNINGS and POST-APPROVAL EXPERIENCE).

ProHeart 12 should not be used more frequently than every 12 months.

The effectiveness of ProHeart 12 has not been evaluated in dogs less than 12 months of age.

Prior to administration of ProHeart 12, dogs should be tested for existing heartworm infections. Infected dogs should be treated with an adulticide to remove adult heartworms. ProHeart 12 is not effective against adult D. immitis.

Caution should be used when administering ProHeart 12 to heartworm positive dogs (see ADVERSE REACTIONS).

ADVERSE REACTIONS

A well-controlled field study was conducted, including a total of 593 dogs (297 received two doses of ProHeart 12, 12 months apart and 296 received a monthly oral heartworm preventive as active control) ranging in age from 1 to 14 years. Over the 605-day study period, all observations of potential adverse reactions were recorded.

Table 2: Number of Dogs* with Adverse Reactions Reported During the ProHeart 12 Field Study

Adverse Reaction | ProHeart® 12; n=297 (%) | Active Control; n=296 (%)
Vomiting | 75 (25.3) | 78 (26.4)
Lethargy | 46 (15.5) | 34 (11.5)
Diarrhea (with and without blood) | 43 (14.5) | 46 (15.5)
Anorexia | 41 (13.8) | 31 (10.5)
Seizures | 10 (3.4) | 7 (2.4)
Hepatopathy | 8 (2.7) | 3 (1.0)
Hypersalivation | 7 (2.4) | 3 (1.0)
Anaphylactoid/Hypersensitivity Reactions | 6 (2.0) | 4 (1.4)

*Some dogs may have experienced more than one adverse reaction or more than one occurrence of the same adverse reaction during the study.

Two ProHeart 12 (moxidectin) - treated dogs experienced anaphylactoid/hypersensitivity-related clinical signs within the first 24 hours following the initial treatment. Both dogs responded to symptomatic treatment. One dog experienced hives and facial swelling that resolved in 24 hours. The second dog experienced redness and swelling of the face and paws, followed by vomiting, polydipsia, and elevated heart rate and was treated symptomatically. Signs resolved within 4 days. One dog was pre-treated before the second injection of ProHeart 12, and neither dog had a reaction to the second dose 12 months later. One active control-treated dog experienced anaphylactoid/hypersensitivity-related clinical signs within the first 24 hours. The dog was withdrawn from the study prior to the second monthly dose.

Mild injection site reactions occurred in six ProHeart 12-treated dogs and were observed from one to seven days post dosing and included warmth, swelling and pruritus. One of these cases included mild pruritus at the injection site that resolved spontaneously within 24 hours of administration.

In a laboratory effectiveness study, dogs with 4- and 6-month-old heartworm infections administered moxidectin microspheres at a dose of 0.17 mg/kg experienced vomiting, lethargy and bloody diarrhea. These signs were more severe in the dogs with 4-month-old heartworm infections, including one dog that was recumbent and required supportive care, than in the dogs with older (6-month-old) infections.

Post-Approval Experience (2018): The following adverse events are based on post-approval adverse drug experience reporting for ProHeart 6. ProHeart 12 and ProHeart 6 are the same formulation, but ProHeart 12 is three times the concentration of ProHeart 6. Not all adverse reactions are reported to FDA/CVM. It is not always possible to reliably estimate the adverse event frequency or establish a causal relationship to product exposure using these data. The following adverse events are listed in decreasing order of frequency by body system.
Immune: anaphylaxis and/or anaphylactoid reactions, urticaria, head/facial edema, pruritus, pale mucous membranes, collapse, cardiovascular shock, erythema, immune-mediated hemolytic anemia, immune-mediated thrombocytopenia (signs reflected in other system categories could be related to allergic reactions, i.e. gastrointestinal, dermatologic, and hematologic)
Gastrointestinal: vomiting (with or without blood), diarrhea with or without blood, hypersalivation
General: depression, lethargy, anorexia, fever, weight loss, weakness
Dermatological: injection site pruritus/swelling, erythema multiforme
Neurological: seizures, ataxia, trembling, hind limb paresis
Hematological: leukocytosis, anemia, thrombocytopenia
Respiratory: dyspnea, tachypnea, coughing
Hepatic: elevated liver enzymes, hypoproteinemia, hyperbilirubinemia, hepatopathy
Urinary: elevated BUN, elevated creatinine, hematuria, polydipsia, polyuria
Cardiopulmonary signs such as coughing and dyspnea may occur in heartworm positive dogs.
In some cases, death has been reported as an outcome of the adverse events listed above.

Foreign market experience with ProHeart 12 includes similar voluntarily reported adverse events, including death, following administration of ProHeart 12.

For a copy of the Safety Data Sheet (SDS) or to report suspected adverse reactions, contact Zoetis at 1-888-963-8471. For additional information about adverse drug experience reporting for animal drugs, contact FDA at 1-888-FDA-VETS or http://www.fda.gov/AnimalVeterinary/SafetyHealth.

Client Information Sheet

ProHeart 12

(moxidectin)

Review this information with your veterinarian each time your dog receives ProHeart 12. When your veterinarian prescribes medicine for your dog, it’s sometimes hard to remember all the information discussed during the visit. This sheet is provided as a summary, but if you have any additional questions you should speak with your veterinarian.

What is ProHeart 12?
ProHeart 12 is a medication that prevents heartworm disease in dogs 12 months of age and older. Your veterinarian gives it to your dog via an injection and it protects your dog from developing heartworm disease for 12 full months. ProHeart 12 also treats common hookworm infections your dog may have at the time of injection.

What should I discuss with my veterinarian before using ProHeart 12?

• General health – ProHeart 12 should only be given to healthy dogs.
• Changes in behavior or health, including weight loss.
• Allergies – Past or present, uncontrolled allergies, including food, flea or skin allergies.
• Past problems with or reactions to vaccines or medications.
• Current medications, supplements or special diets, including those you can get without a prescription.

What is heartworm disease and how can my dog get it?
Heartworm disease is a serious, potentially fatal illness where worms grow in a dog’s heart and lungs. Mosquitoes spread heartworm disease when they bite a dog. A single bite from an infected mosquito can put your dog at risk for developing heartworm disease.

What are hookworms and how could my dog get them?
Hookworms are common parasites that can live in a dog’s intestines. Your dog can get hookworms by eating hookworm larvae (young hookworms) that may be in the dirt or they can get hookworms through skin contact.

What possible ProHeart 12 side effects could happen to my dog?
It is important to contact your veterinarian if you observe any signs of illness in your dog. Severe reactions require emergency treatment by your veterinarian. Watch your dog for the following possible signs of illness:
• Allergic reactions - Allergic symptoms such as swelling of the face, itching, hives and/or inflamed skin. Allergic reactions may occur when ProHeart 12 is given alone or with vaccines. Some allergic reactions can be severe, such as difficulty breathing or collapse.
• Vomiting and/or diarrhea - Either with or without blood.
• Seizures
• Change in your dog's appetite or activity level
Most reactions occur within the first 24 hours of receiving ProHeart 12; severe allergic reactions may occur in the first two hours.
IF YOU NOTICE ANY SIGNS OF ILLNESS, OR ANYTHING OUT OF THE ORDINARY AFTER YOUR DOG RECEIVES PROHEART 12, CONTACT YOUR VETERINARIAN IMMEDIATELY.
In some cases, these events may be serious and may cause death.

If you have any questions about ProHeart 12, talk to your veterinarian.
[Veterinarian: Please place contact information below]
Practice Name:
Vet Name:
Phone:
To obtain additional information, visit ProHeart12.com or call 1-888-963-8471.
Approved by FDA under NADA # 141-519

zoetis
Distributed by: Zoetis Inc. Kalamazoo, MI 49007
All trademarks are the property of Zoetis Services LLC or a related company or a licensor unless otherwise noted.
© 2019 Zoetis Services LLC. All rights reserved. PHT-00XXX

INFORMATION FOR DOG OWNERS

Always provide Client Information Sheet and review with owners before administering ProHeart 12. Owners should be advised of the potential for adverse reactions, including anaphylaxis, and be informed of the clinical signs associated with drug toxicity (see WARNINGS, ADVERSE REACTIONS and POST-APPROVAL EXPERIENCE sections.)
Owners should be advised to contact their veterinarian immediately if signs of toxicity are observed. The vast majority of patients with drug related adverse reactions have recovered when the signs are recognized and veterinary care, if appropriate, is initiated.

CLINICAL PHARMACOLOGY

Moxidectin is a semi-synthetic methoxime derivative of nemadectin which is a fermentation product of Streptomyces cyaneogriseus subspecies noncyanogenus. Moxidectin is a pentacyclic 16-membered lactone macrolide.

Moxidectin has activity resulting in paralysis and death of affected parasites. The stage of the canine heartworm affected at the recommended dose rate of 0.5 mg/kg (0.23 mg/lb) is the tissue larval stage. The larval and adult stages of the canine hookworms, A. caninum and U. stenocephala, are susceptible.

Following injection with ProHeart 12, peak moxidectin blood levels will be observed approximately 7-14 days after treatment. At the end of the 12-month dosing interval, residual drug plasma concentrations are negligible. Accordingly, little or no drug accumulation is expected to occur with repeated administrations.

EFFECTIVENESS

Prevention of Heartworm:
In two separate well-controlled laboratory studies, ProHeart 12 administered at a dose of 0.5 mg/kg (0.23 mg/lb), demonstrated 100% effectiveness in preventing the development of D. immitis in dogs inoculated with infective larvae 365 days after treatment.

In a well-controlled 605-day US field study, two doses of ProHeart 12 were administered subcutaneously at a dosage of 0.5 mg/kg (0.23 mg/lb), 12 months apart. A total of 235, 226 and 222 ProHeart 12-treated dogs completed the heartworm testing (adult heartworm antigen and microfilariae) on Days 365, 480 and 605, respectively. None of these dogs tested positive for heartworm on any of the test days.

Treatment of Existing Larval and Adult Hookworms:
Seven well-controlled laboratory studies conducted with moxidectin microspheres at a dose of 0.17 mg/kg confirm the effectiveness against natural infections and induced infections of larval and adult A. caninum and U. stenocephala. All studies demonstrated ≥ 90% effectiveness against the respective hookworm species.

ANIMAL SAFETY

Margin of Safety: ProHeart 12 was subcutaneously administered to Beagle dogs (8 dogs per group) at 1X, 3X, and 5X the recommended dose of 0.5 mg/kg body weight on Days 1, 183, and 365. The control group (8 dogs) received saline injections. ProHeart 12 was well tolerated and did not result in any adverse systemic effects. ProHeart 12-related findings included edema and thickening of the injection site.

Ivermectin-Sensitive Collie Safety: In a laboratory study, 15 ivermectin-sensitive Collie dogs in three treatment groups were administered one dose of saline and one dose of ProHeart 12, 21 days apart. Each dog served as its own control and the order of administration of the saline and ProHeart 12 varied by treatment group. ProHeart 12 was dosed at 0.5 mg/kg body weight (1X, five dogs), 1.5 mg/kg body weight (3X, five dogs), or 2.5 mg/kg body weight (5X, five dogs). No clinical signs of moxidectin toxicity were observed during the 42-day study.

Heartworm-Positive Safety: In a laboratory study, 16 Beagle dogs implanted with adult heartworms (D. immitis) received either ProHeart 12 at 1.5 mg/kg body weight (3X, 8 dogs) or a saline injection (control, 8 dogs). At 119 days post-infection (56 days post-moxidectin treatment), no adverse clinical signs and no gross pathological effects were noted in dogs with induced adult heartworm infections.

Reproductive Safety:
Females: A reproductive laboratory study in 40 female Beagle dogs assessed the safety of ProHeart 12 at a single 1.5 mg/kg body weight (3X) dose. The dogs were divided into four treatment groups of 8 dogs per group to cover the critical periods of the reproductive cycle (pre-mating, mating, mid-gestation, and lactation). The control group (8 dogs) were untreated. No adverse effects in terms of conception, pregnancy maintenance, and the development, growth, and health of the puppies were observed through puppy weaning at 6 weeks of age.
Males: A reproductive laboratory study assessed the safety of ProHeart 12 in eight male Beagle dogs at a single 1.5 mg/kg body weight (3X) dose. The control group (8 dogs) received a saline injection. No adverse reactions were noted in any of the dogs during the 91-day study. No clinically significant changes or abnormalities were noted in semen quality. Minor injection site thickening was noted by palpation in four dogs; all resolved within 13 weeks.

CONSTITUTION PROCEDURES

ProHeart 12 must be prepared at least 30 minutes prior to the first use.
Items needed to constitute ProHeart 12 10 mL (889 mg) product (9 mL when constituted):
• Sterile vehicle vial- included
• Microspheres vial- included
• Vent needle (25G)- included
• Sterile 10 mL syringe for transfer- not included
• Transfer needle (18G or 20G) - not included

Constitution of the 10 mL vial product.
1. Shake the microsphere vial to break up any aggregates prior to constitution.
2. Using an 18G or 20G needle and sterile syringe withdraw 8 mL of the unique sterile vehicle from the vial.
There is more sterile vehicle supplied than the 8 mL required.
3. Insert the enclosed 25G vent needle into the microsphere vial.
4. Slowly transfer the 8 mL of sterile vehicle into the microsphere vial through the stopper using the transfer needle and syringe.
5. Once the sterile vehicle has been added, remove the vent and transfer needles from the microsphere vial.
Discard unused sterile vehicle and needles.
6. Shake the microsphere vial vigorously until a thoroughly mixed suspension is produced.
The product may appear as a hazy to milky suspension.
7. Record the time and date of mixing on the microsphere vial.
8. Allow suspension to stand for at least 30 minutes to allow large air bubbles to dissipate.
9. Before every use, gently swirl the mixture to achieve uniform suspension. The product may appear as a hazy to milky suspension.
The microspheres and vehicle will gradually separate on standing.
10. Use a 1 mL or 3 mL syringe and an 18G or 20G needle for dosing. Dose promptly after drawing into dosing syringe.
If administration is delayed, gently roll the dosing syringe prior to injection to maintain a uniform suspension and accurate dosing.
11. Refrigerate the unused product. The constituted product remains stable for 8 weeks in a refrigerator.
Avoid direct sunlight.

STORAGE INFORMATION

Store the unconstituted product at or below 25°C (77°F). Do not expose to light for extended periods of time. After constitution, the product is stable for 8 weeks stored under refrigeration at 2° to 8°C (36° to 46°F).

HOW SUPPLIED

ProHeart 12 10 mL vial product is available in the following package sizes.

1-Pack | 5-Pack | 10-Pack
1 - 10% moxidectin sterile microspheres- 889 mg/vial 1 - Sterile vehicle - 8 mL/vial | 5 - 10% moxidectin sterile microspheres- 889 mg/vial 5 - Sterile vehicle - 8 mL/vial | 10 - 10% moxidectin sterile microspheres- 889 mg/vial 10 - Sterile vehicle - 8 mL/vial

zoetis
Distributed by: Zoetis Inc., Kalamazoo, MI 49007
Revised: November 2021
Approved by FDA under NADA # 141-519
40036952